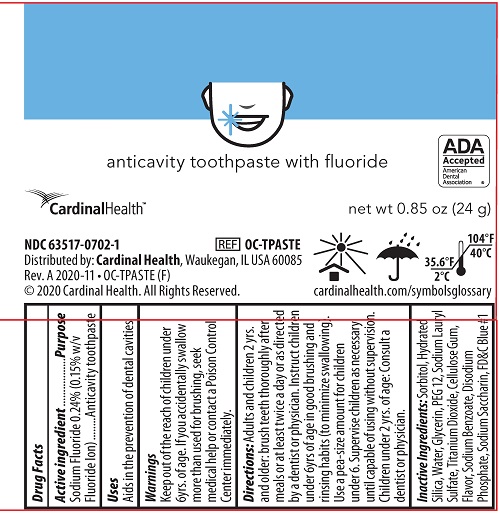 DRUG LABEL: Cardinal Health
NDC: 63517-070 | Form: PASTE, DENTIFRICE
Manufacturer: Cardinal Health 200, LLC
Category: otc | Type: HUMAN OTC DRUG LABEL
Date: 20240618

ACTIVE INGREDIENTS: SODIUM FLUORIDE 0.15 g/100 g
INACTIVE INGREDIENTS: MINT; POLYETHYLENE GLYCOL 600; HYDRATED SILICA; SODIUM LAURYL SULFATE; TITANIUM DIOXIDE; CARBOXYMETHYLCELLULOSE SODIUM; SODIUM BENZOATE; SACCHARIN SODIUM; FD&C BLUE NO. 1; SORBITOL; GLYCERIN; SODIUM PHOSPHATE, DIBASIC, DIHYDRATE; WATER

Cardinal Health Toothpaste

Active ingredient

Sodium Fluoride 0.24% (0.15% w/v Fluoride Ion)

Purpose

Anticavity toothpaste

Uses

Aids in the prevention of dental cavities

KEEP OUT OF REACH OF CHILDREN

Keep out of the reach of children under 6yrs. of age. If you accidentally swallow more than used for brushing, seek medical help or contact a Poison Control Center immediately.

Directions:

Adults and children 2 yrs. and older: brush teeth thoroughly after meals or at least twice a day or directed by a dentist or physician. Instruct children under 6yrs of age in good brushing and rinsing habits (to minimize swallowing). Use a pea-size amount for children under 6. Supervise children as necessary until capable of using without supervision. Children under 2 yrs. of age: Consult a dentist or physician.

Inactive Ingredients:

Sorbitol, Hydrated Silica, Water, Glycerin, PEG 12, Sodium Lauryl Sulfate, Titanium Dioxide, Cellulose Gum, Flavor, Sodium Benzoate, Disodium Phosphate, Sodium Saccharin, FD&C Blue #1

Principal Display

anticavity toothpaste with fluoride

ADA Accepted American Dental Association

Cardinal Health™

net wt 0.85 oz (24 g)

NDC 63517-0702-1

REF OC-TPASTE

Distributed by: Cardinal Health, Waukegan, IL USA 60085

Rev.A 2020-11 • OC-TPASTE (F)

© 2020 Cardinal Health. All Rights Reserved.

cardinalhealth.com/symbolsglossary